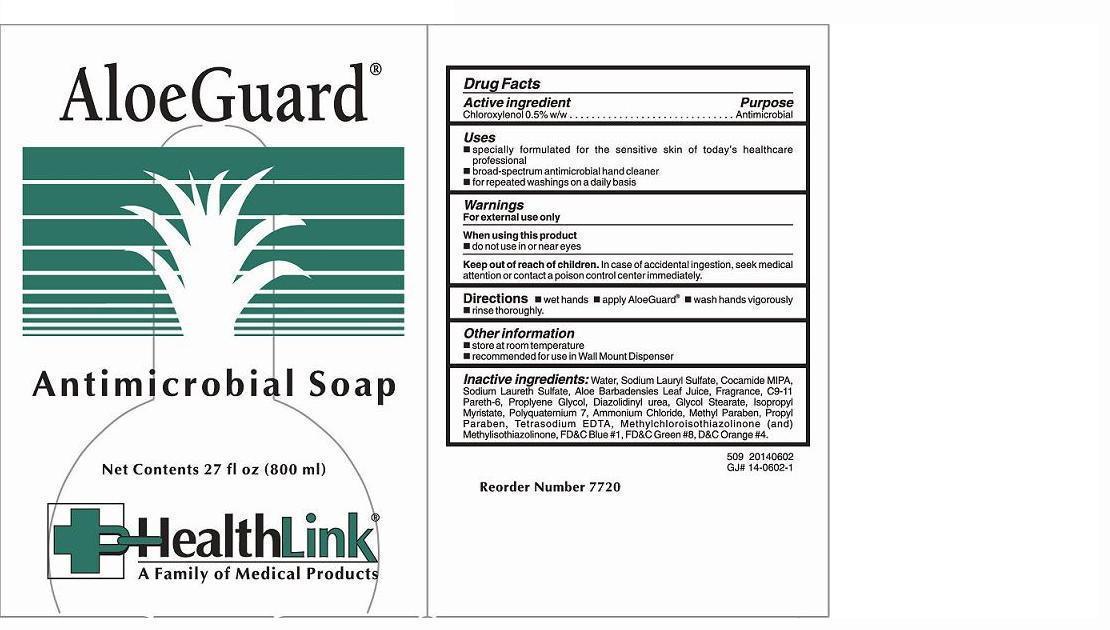 DRUG LABEL: ALOEGUARD ANTIMICROBIAL
NDC: 63843-509 | Form: SOAP
Manufacturer: HealthLink
Category: otc | Type: HUMAN OTC DRUG LABEL
Date: 20180131

ACTIVE INGREDIENTS: CHLOROXYLENOL 5 g/1000 mL
INACTIVE INGREDIENTS: WATER; SODIUM LAURYL SULFATE; COCO MONOISOPROPANOLAMIDE; SODIUM LAURETH SULFATE; ALOE VERA LEAF; C9-11 PARETH-6; PROPYLENE GLYCOL; DIAZOLIDINYL UREA; GLYCOL STEARATE; ISOPROPYL MYRISTATE; POLYQUATERNIUM-7 (70/30 ACRYLAMIDE/DADMAC; 1600000 MW); AMMONIUM CHLORIDE; METHYLPARABEN; PROPYLPARABEN; EDETATE SODIUM; METHYLCHLOROISOTHIAZOLINONE; METHYLISOTHIAZOLINONE

Drug Facts Active ingredient

Chloroxylenol 0.5% w/w

Purpose

Antimicrobial

Keep out of reach of children

In case of accidental ingestion, seek medical attention or contact a poison control center immediately.

Uses

 Specially formulated for the sensitive skin of today's healthcare professional
 broad-spectrum antimicrobial hand cleaner
 for repeated washings on a daily basis

Warnings

For external use only When using this product  do not use in or near eyes Keep out of reach of children. In case of accidental ingestion, seek medical attention or contact a poison control center immediately.

Directions

 wet hands  apply AloeGuard  wash hands vigorously  rinse thoroughly.

Other information

 store at room temperature

Inactive ingredients:

Water, Sodium Lauryl Sulfate, Cocamide MIPA, Sodium Laureth Sulfate, Aloe Barbadensis Leaf Juice, Fragrance, C9-11 Pareth-6, Proplyene Glycol, Diazolidinyl Urea, Glycol Stearate, Isopropyl Myristate, Polyquaternium 7, Ammonium Chloride, Methyl Paraben, Propyl Paraben, Tetrasodium EDTA, Methylchloroisothiazolinone (and) Methylisothiazolinone, FD&C Blue #1, FD&C Green #8, D&C Orange #4.